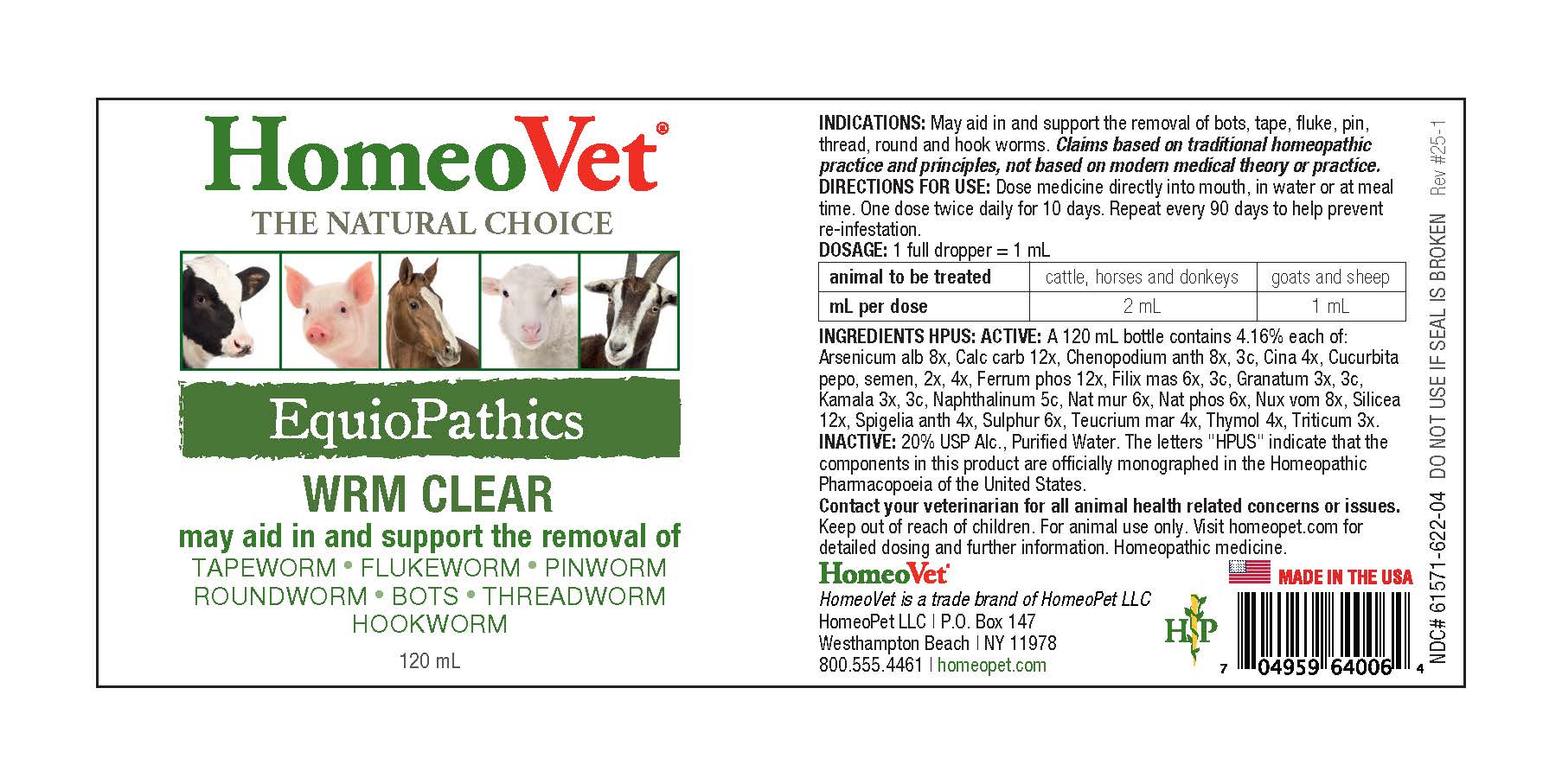 DRUG LABEL: EquioPathics Wrm Clear
NDC: 61571-622 | Form: LIQUID
Manufacturer: HomeoPet, LLC
Category: homeopathic | Type: OTC ANIMAL DRUG LABEL
Date: 20251216

ACTIVE INGREDIENTS: ARSENIC TRIOXIDE 8 [hp_X]/120 mL; OYSTER SHELL CALCIUM CARBONATE, CRUDE 12 [hp_X]/120 mL; CHENOPODIUM AMBROSIOIDES  8 [hp_X]/120 mL; ARTEMISIA CINA FLOWER 4 [hp_X]/120 mL; PUMPKIN SEED 2 [hp_X]/120 mL; FERROSOFERRIC PHOSPHATE 12 [hp_X]/120 mL; DRYOPTERIS FILIX-MAS ROOT 6 [hp_X]/120 mL; PUNICA GRANATUM ROOT BARK 3 [hp_X]/120 mL; KAMALA 3 [hp_X]/120 mL; SODIUM CHLORIDE 6 [hp_X]/120 mL; SODIUM PHOSPHATE, DIBASIC, HEPTAHYDRATE 6 [hp_X]/120 mL; NAPHTHALENE 5 [hp_C]/120 mL; STRYCHNOS NUX-VOMICA SEED 8 [hp_X]/120 mL; SILICON DIOXIDE 12 [hp_X]/120 mL; SPIGELIA ANTHELMIA 4 [hp_X]/120 mL; SULFUR 6 [hp_X]/120 mL; TEUCRIUM MARUM 4 [hp_X]/120 mL; THYMOL  4 [hp_X]/120 mL; ELYMUS REPENS TOP 3 [hp_X]/120 mL
INACTIVE INGREDIENTS: ALCOHOL; WATER

EquioPathics Wrm Clear

EquioPathics Wrm Clear

may aid and support the removal of

TAPEWORM-FLUKEWORM-PINWORM

ROUNDWORM-BOTS-THREADWORM-HOOKWORM

DIRECTIONS FOR USE AND DOSAGE

Dose medicine directly into mouth, in water or at meal time. One dose twice daily for 10 days. Repeat every 90 days to help prevent re-infestation.

animal to be treated | cattle, horses and donkeys | goats and sheep
mL per dose | 2 mL | 1 mL

INDICATIONS

May aid in and support the removal of bots, tape, fluke, pin, thread, round and hook worms. Claims based on traditional homeopathic practice and principes, not based on modern medical theory or practice.

Ingredients HPUS:ACTIVE

Arsencium alb 8x, Calc carb 12x, Chenopodium anth 8x, 3c, Cina 4x, Cucurbita pepo, semen 2x, 4x, Ferrum phos 12x, Filix mas 6x, 3x, Granatum 3x, 3c, Kamala 3x, 3c, Naphthalinum 5c, Nat mur 6x, Nat phos 6x, Nux vom 8x, Silicea 12x, Spigelia anth 4x, Sulphur 6x, Teucrium mar 4x, Thymol 4x, Triticum 3x.

Inactive Ingredients

USP Alcohol, Purified Water